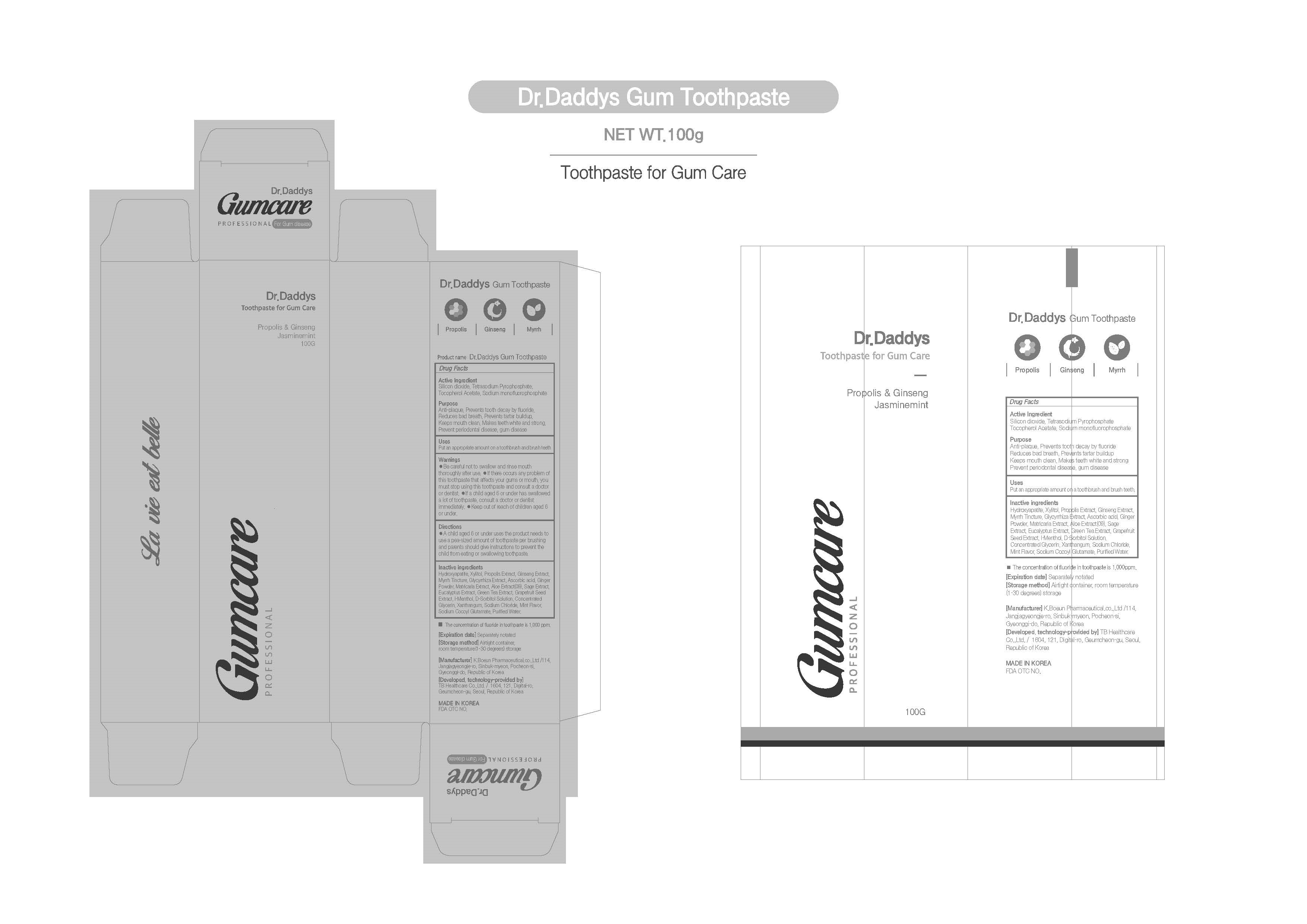 DRUG LABEL: Dr. DADDYS GumToothpaste
NDC: 76884-0012 | Form: PASTE, DENTIFRICE
Manufacturer: TB Healthcare Co., Ltd.
Category: otc | Type: HUMAN OTC DRUG LABEL
Date: 20220413

ACTIVE INGREDIENTS: .ALPHA.-TOCOPHEROL ACETATE 0.2 g/100 g; SILICON DIOXIDE 17 g/100 g; SODIUM PYROPHOSPHATE 0.5 g/100 g; SODIUM MONOFLUOROPHOSPHATE 0.76 g/100 g
INACTIVE INGREDIENTS: XYLITOL; WATER

ACTIVE INGREDIENT

Silicon Dioxidel,Tetrasodium Pyrophosphate,Tocopherol Acetate,Sodium Monofluorophosphate

INACTIVE INGREDIENT

D-Sorbitol Solution,Concentrated Glycerin,Xanthan gum,Sodium Cocoyl Glutamate,Ascorbic Acid,Hydroxyapatite,Xylitol,Sodium
Chloride,Grapefruit Seed Extract,Glycyrrhiza Extract,Green Tea Extract,Matricaria Extract,Sage Extract,Aloe
Extract,Eucalyptus Extract,Ginseng Extract,Propolis Extract,Ginger Powder,Myrrh Tincture,l-Menthol,Flavor,Water

PURPOSE

Reduces bad breath, Prevents tartar buildup, Keeps mouth clean, Makes teeth white and strong, Prevent periodontal disease, gum disease

Keep out of reach of children

INDICATIONS AND USAGE

Put an appropriate amount on a toothbrush and brush teeth

WARNINGS

1. Be careful not to swallow. Rinse mouth thoroughly after use

2. If the use of toothpaste causes abnormalities such as gums or mouth injury, discontinue use and consult a doctor or dentist.

3. For children under 6 years of age, use a small amount of toothpaste as small as pea per use, and use under the guidance of a guardian to avoid sucking or swallowing.

4. If a child under 6 years old swallows large amount, consult with a doctor or dentist immediately.

5. Keep out of the reach of children under 6 years of age.

DOSAGE AND ADMINISTRATION

For dental use only